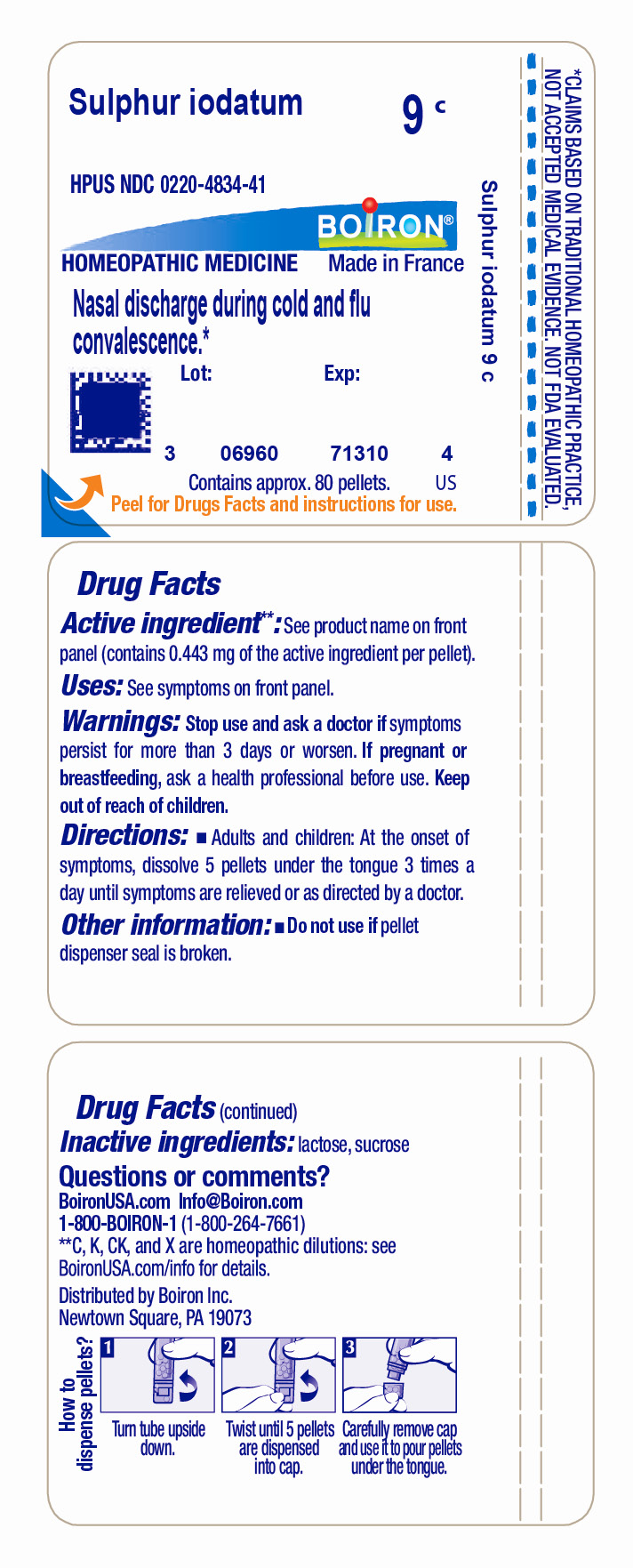 DRUG LABEL: Sulphur iodatum
NDC: 0220-4834 | Form: PELLET
Manufacturer: Boiron
Category: homeopathic | Type: HUMAN OTC DRUG LABEL
Date: 20231115

ACTIVE INGREDIENTS: SULFUR IODIDE 9 [hp_C]/9 [hp_C]
INACTIVE INGREDIENTS: SUCROSE; LACTOSE, UNSPECIFIED FORM

Sulphur iodatum 9C

ACTIVE INGREDIENT

Sulphur iodatum 9C
(**contains 0.443 mg of the active ingredient per pellet)

INDICATIONS AND USAGE

Nasal Discharge During Cold And Flu Convalescence*

Stop use and ask a doctor if symptoms persist for more than 3 days or worsen

PREGNANCY OR BREAST FEEDING

If pregnant or breast-feeding ask a health professional before use

Keep out of reach of children

INACTIVE INGREDIENT

lactose, sucrose

DOSAGE AND ADMINISTRATION

Adults and children: At the onset of symptoms, dissolve 5 pellets under the tongue 3 times a day until symptoms are relieved or as directed by a doctor.

QUESTIONS

1-800-BOIRON-1 (1-800-264-7661),
BoironUSA.com Info@boiron.com
Distributed by Boiron, Inc. Newtown Square, PA 19073